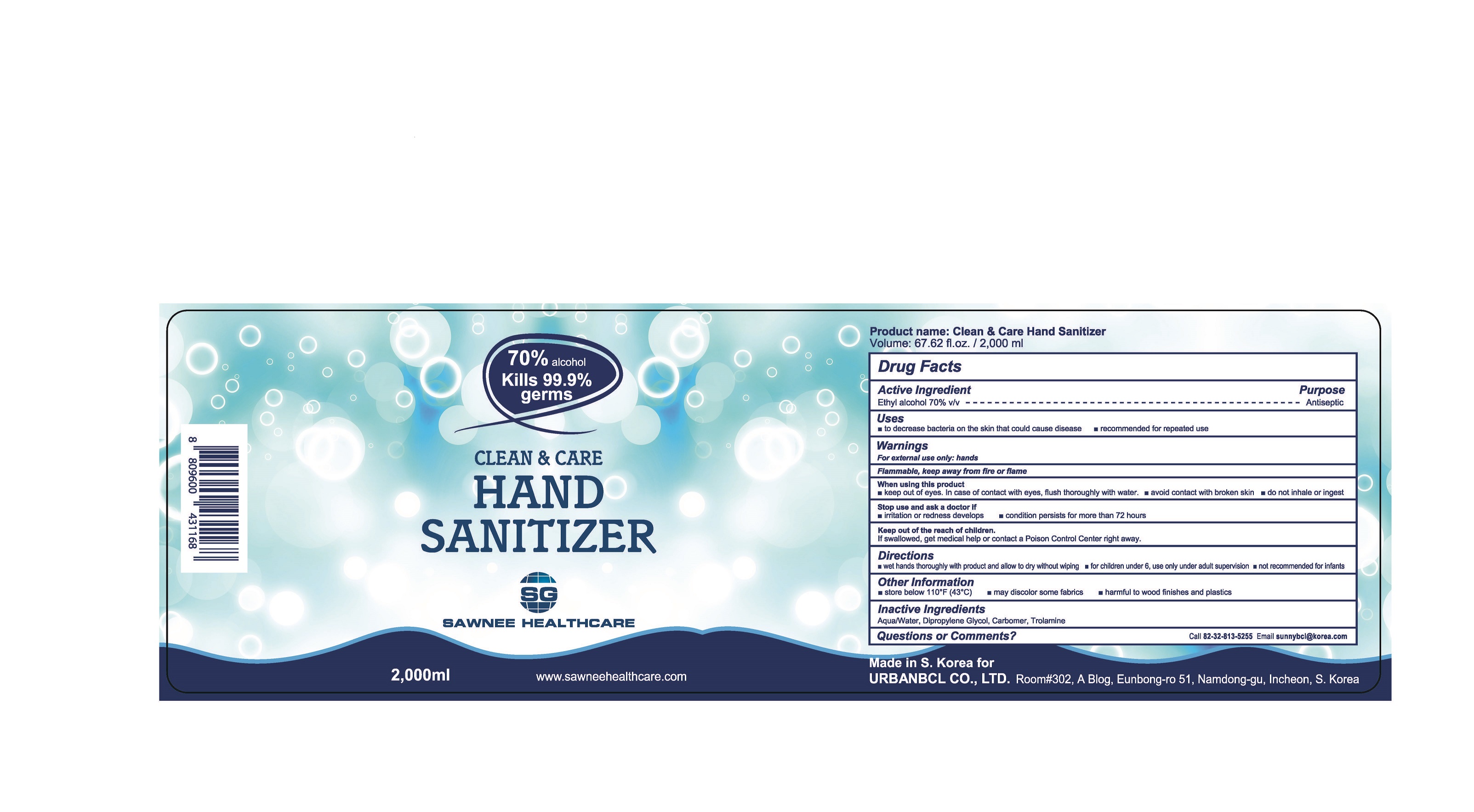 DRUG LABEL: Clean Care Hand Sanitizer
NDC: 74200-0028 | Form: GEL
Manufacturer: URBANBCL CO LTD
Category: otc | Type: HUMAN OTC DRUG LABEL
Date: 20200612

ACTIVE INGREDIENTS: ALCOHOL 70 mL/100 mL
INACTIVE INGREDIENTS: TROLAMINE; WATER; DIPROPYLENE GLYCOL; GLYCERIN

Drug Facts

ACTIVE INGREDIENT

ethyl alcohol

PURPOSE

to decrease bacteria on the skin that could cause disease

recommended for repeated use

KEEP OUT OF REACH OF THE CHILDREN

WARNINGS

■ Flammable. Keep away from fire or flame.

■ For external use only.

■ Do not use in eyes.

■ lf swallowed, get medical help promptly.

■ Stop use, ask doctor lf irritation occurs.

■ Keep out of reach of children.

DOSAGE AND ADMINISTRATION

for external use only

INACTIVE INGREDIENT

Acrylates/C10-30 Alkyl Acrylate Crosspolymer
Trolamine
Glycerin
Dipropylene Glycol
Water

INDICATIONS AND USAGE

wet hands thoroughly with product and allow to dry without wiping

for children under 6, use only under adult supervision

not recommended for infants